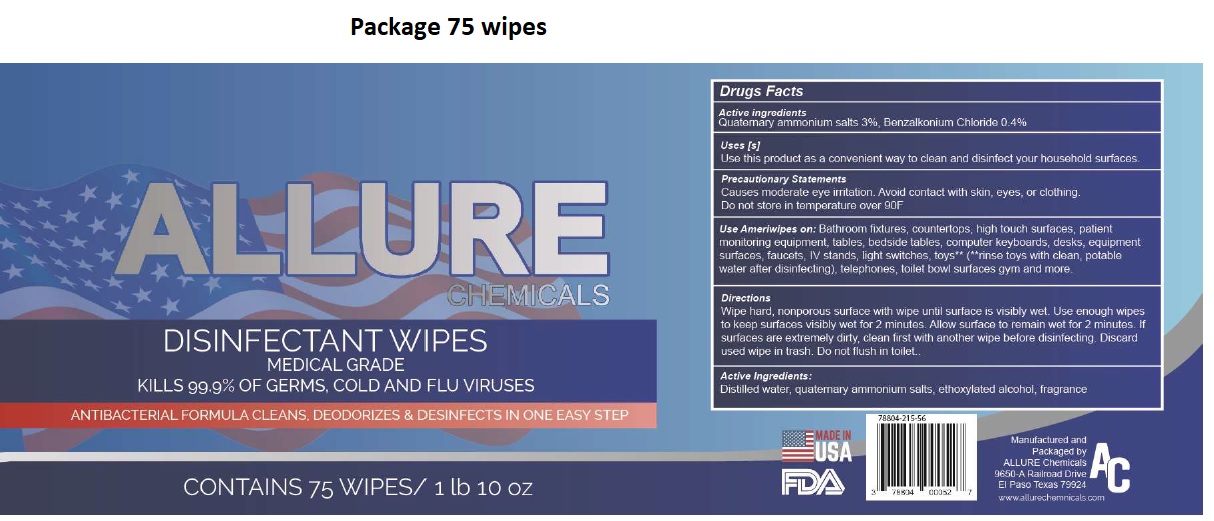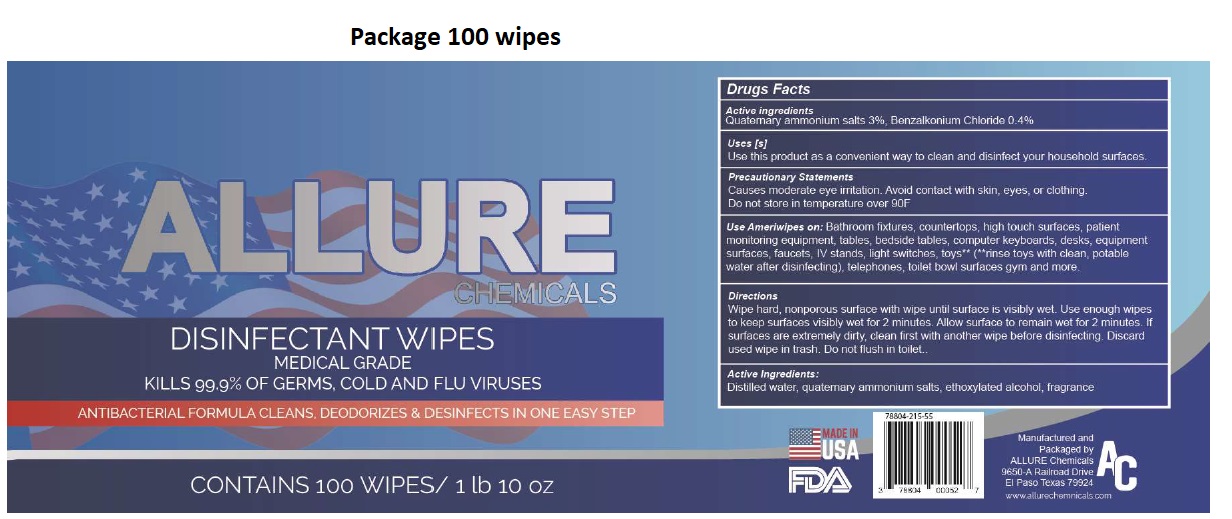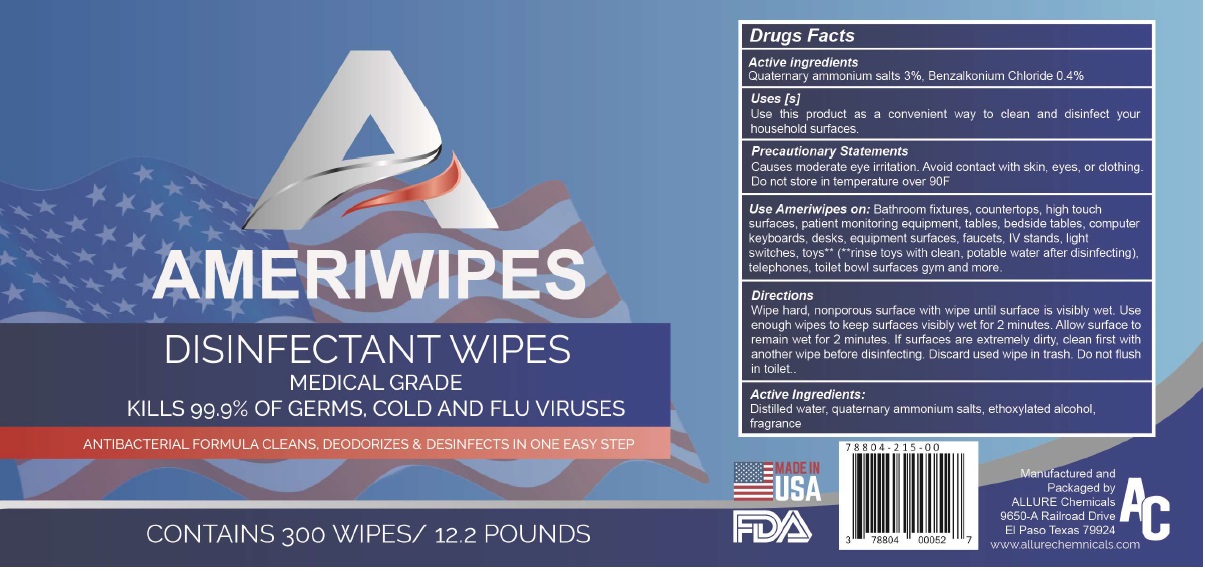 DRUG LABEL: AMERIWIPES DISINFECTANT WIPES
NDC: 78804-215 | Form: CLOTH
Manufacturer: Allure Chemicals LP
Category: otc | Type: HUMAN OTC DRUG LABEL
Date: 20200910

ACTIVE INGREDIENTS: BENZALKONIUM CHLORIDE 0.4 g/100 g
INACTIVE INGREDIENTS: WATER; C20-40 PARETH-3

AMERIWIPES DISINFECTANT WIPES

Active ingredients

Quaternary ammonium salts 3%, Benzalkonium Chloride 0.4%

Purpose

Antiseptic

Use[s]

Use this product as a convenient way to clean and disinfect your household surfaces.

Precautionary Statements

Causes moderate eye irritation. Avoid contact with skin, eyes, or clothing. Do not store in temperature over 90F

Keep out of reach of children.

Use Ameriwipes on: Bathroom fixtures, countertops, high touch surfaces, patient monitoring equipment, tables, beside tables, computer keyboards, desks, equipment surfaces, faucets, IV stands, light switches, toys** (** rinse toys with clean, potable water after disinfecting), telephones, toilet bowl surfaces gym and more.

Directions

Wipe hard, nonporous surface with wipe until surface is visibly wet. Use enough wipes to keep surfaces visibly wet for 2 minutes. Allow surface to remain wet for 2 minutes. If surfaces are extremely dirty, clean first with another wipe before disinfecting. Discard used wipe in trash. Do not flush in toilet.

Inactive ingredients

Distilled Water, quaternary ammonium salts, ethoxylated alcohol, fragrance

MEDICAL GRADE

KILLS 99.9% OF GERMS, COLD AND FLU VIRUSES

ANTIBACTERIAL FORMULA CLEANS, DEODORIZES & DESINFECTS IN ONE EASY STEP

12.2 POUNDS

MADE IN USA

Manufactured and Packaged by

ALLURE Chemicals

9650-A Railroad Drive

EI Paso Texas 79924

www.allurechemnicals.com